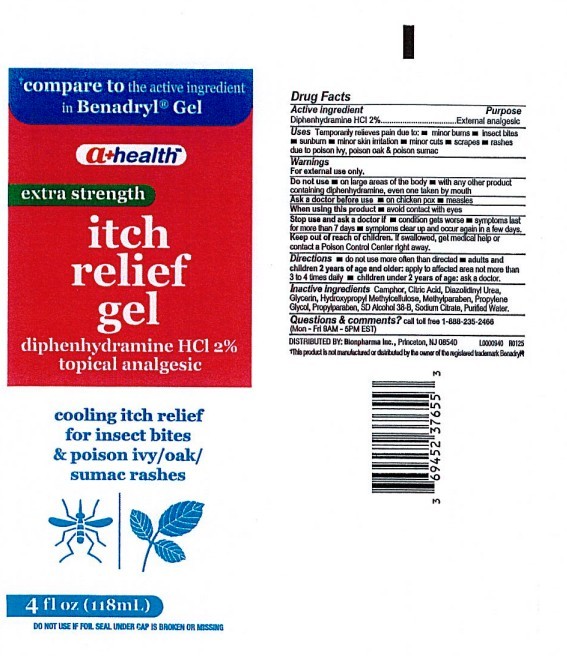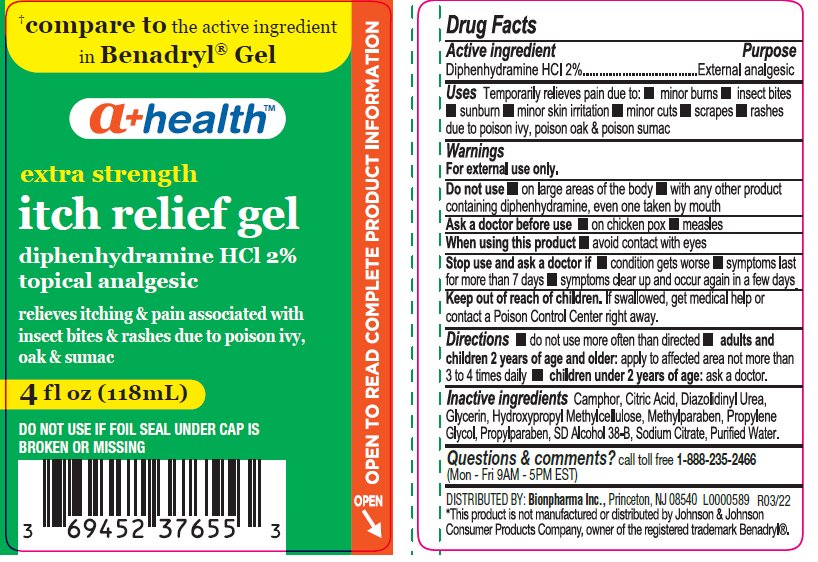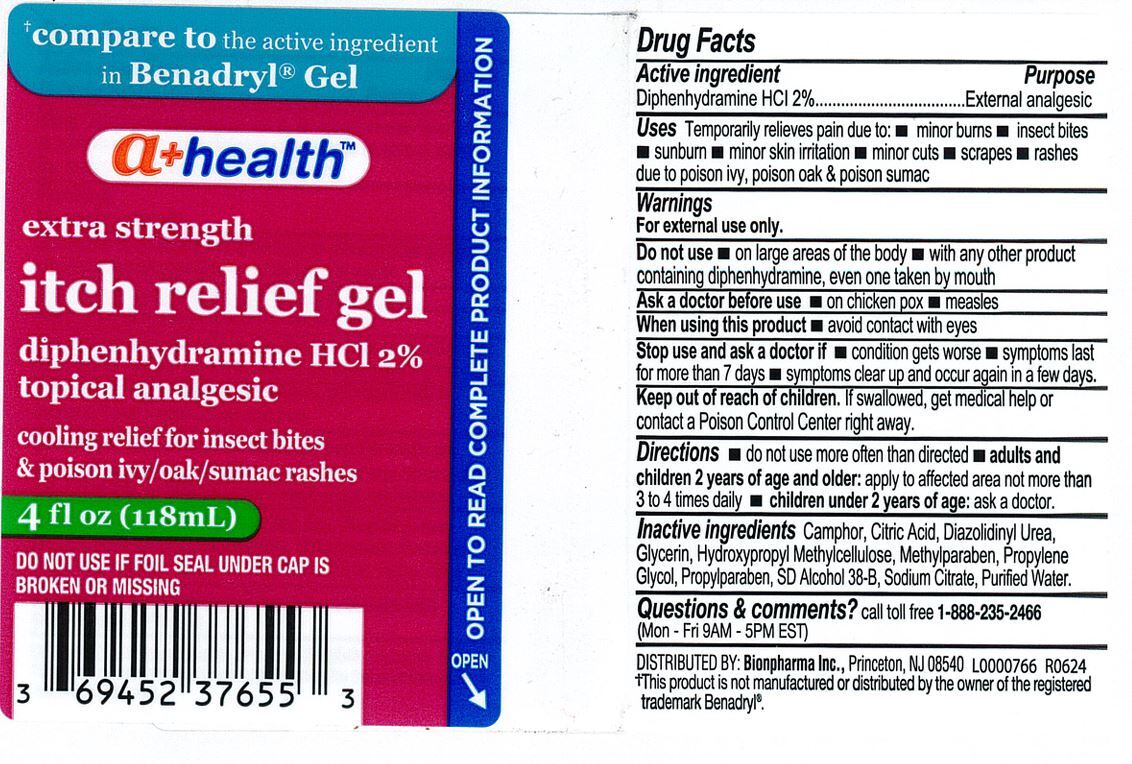 DRUG LABEL: A Health Itch Relief Gel
NDC: 69452-376 | Form: GEL
Manufacturer: Bionpharma, Inc.
Category: otc | Type: HUMAN OTC DRUG LABEL
Date: 20251218

ACTIVE INGREDIENTS: DIPHENHYDRAMINE HYDROCHLORIDE 2 mg/100 mL
INACTIVE INGREDIENTS: METHYLPARABEN; PROPYLPARABEN; PROPYLENE GLYCOL; ALCOHOL; DIAZOLIDINYL UREA; SODIUM CITRATE; WATER; GLYCERIN; ANHYDROUS CITRIC ACID; CAMPHOR (SYNTHETIC); HYPROMELLOSE, UNSPECIFIED

A+ Health Itch Relief Gel

Do not use more often than directed.

Adults and children 2 years of age and older: apply to affected area not more than 3 to 4 times daily.

Children under 2 years of age: ask a doctor.

WARNINGS

For external use only.

INACTIVE INGREDIENT

Camphor, Citric Acid, Diazolidnyl Urea, Glycerin, Hydroxypropyl Methylcellulose, Methylparaben, Propylene Glycol, Propylparaben, SD Alcohol 38-B, Sodium Citrate, Purified Water.

INDICATIONS AND USAGE

Temporarily relieves pain due to: Minor burns, insect bites, sunburn, minor skin irritation, minor cuts, scrapes, rashes due to poison ivy, poison oak and poison sumac.

Keep out of reach of children. If swallowed, get medical help or contact a Poison Control Center right away.

PURPOSE

External Analgesic

ACTIVE INGREDIENT

Diphenhydramine HCl 2%